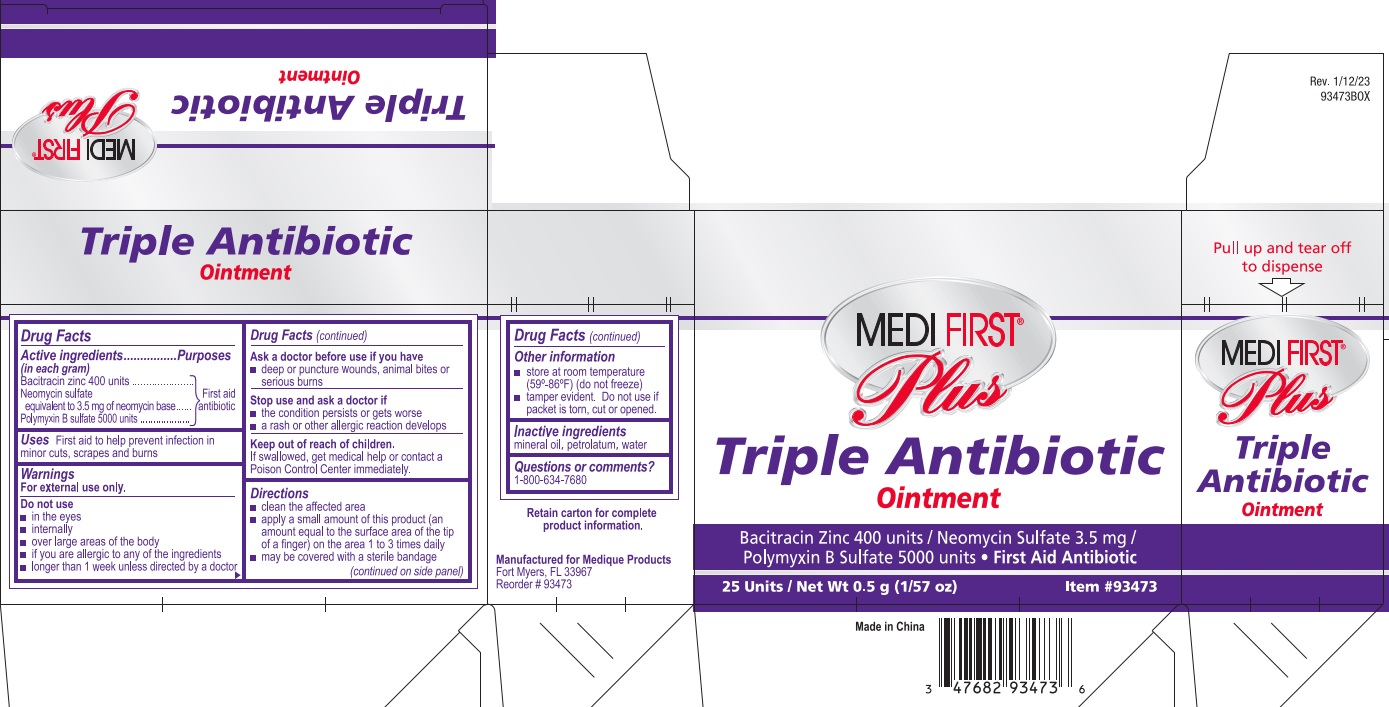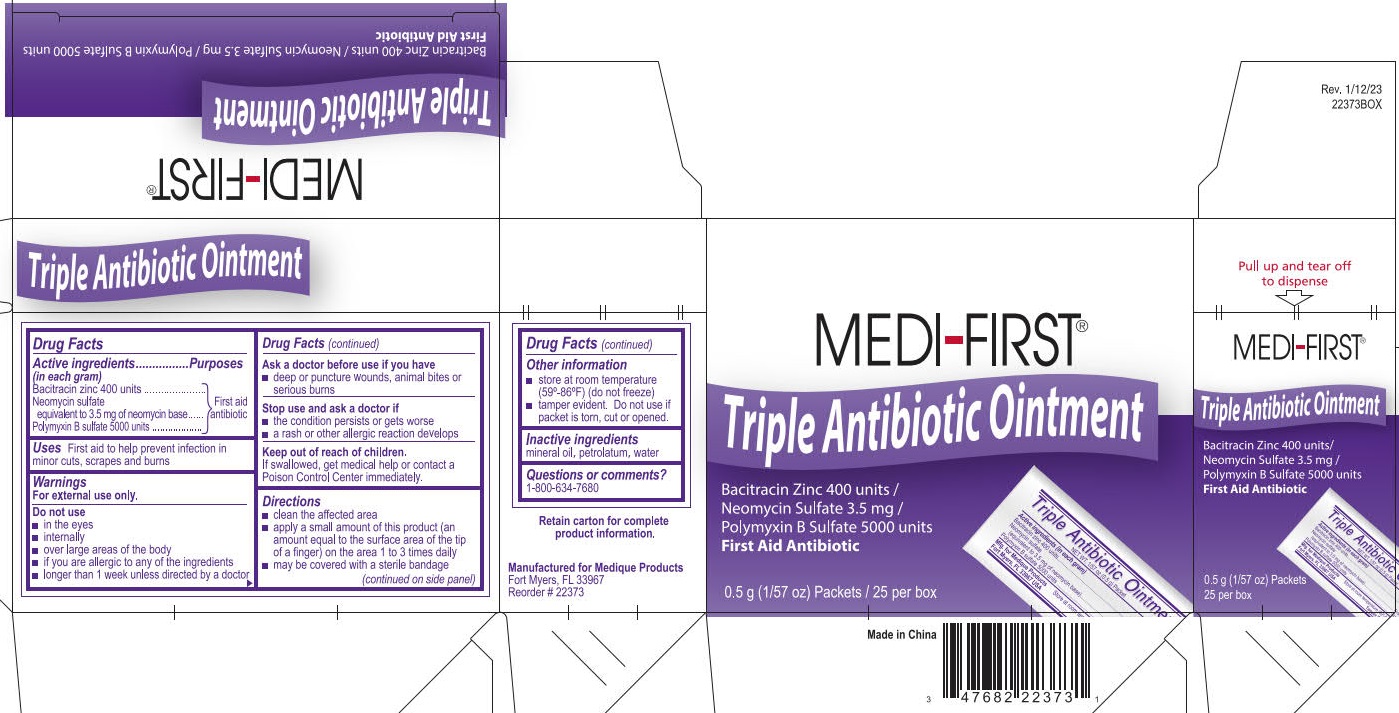 DRUG LABEL: Medi-First Triple Antibiotic
NDC: 47682-982 | Form: OINTMENT
Manufacturer: Unifirst First Aid Corporation
Category: otc | Type: HUMAN OTC DRUG LABEL
Date: 20250909

ACTIVE INGREDIENTS: BACITRACIN ZINC 400 [iU]/1 g; NEOMYCIN SULFATE 3.5 mg/1 g; POLYMYXIN B SULFATE 5000 [iU]/1 g
INACTIVE INGREDIENTS: WATER; MINERAL OIL; PETROLATUM

Medi-First Triple Antibiotic Ointment

Drug Facts

Active ingredients (in each gram)

Bacitracin zinc 400 units

Neomycin sulfate

equivalent to 3.5 mg neomycin base

Polymyxin B sulfate 5000 units

Purposes

First aid antibiotic

First aid antibiotic

First aid antibiotic

Uses

First aid to help prevent infection in minor cuts, scrapes and burns

Warnings

For external use only.

Do not use

- in the eyes
- internally
- over large areas of the body
- if you are allergic to any of the ingredients
- longer than 1 week unless directed by a doctor

Ask a doctor before use if you have

- deep or puncture wounds, animal bites or serious burns

Stop use and ask a doctor if

- the condition persists or gets worse
- a rash or other allergic reaction develops

Keep out of reach of children.

If swallowed, get medical help or contact a Poison Control Center immediately.

Directions

- clean the affected area
- apply a small amount of this product (an amount equal to the surface area of the tip of a finger) on the area 1 to 3 times daily
- may be covered with a sterile bandage

Other information

- store at room temperature (59º-86°F) (do not freeze)
- tamper evident. Do not use if packet is torn, cut or opened.

Inactive ingredients

mineral oil, petrolatum, water

Questions or comments? 1-800-634-7680

PACKAGE LABEL

Medi-First®

Triple Antibiotic Ointment

Bacitracin Zinc 400 units /

Neomycin Sulfate 3.5 mg /

Polymyxin B Sulfate 5000 units

First Aid Antibiotic

0.5 g (1/57 oz) Packets / 25 per box

Made in China

PACKAGE LABEL

Medi-First® Plus

Triple Antibiotic Ointment

Bacitracin Zinc 400 units / Neomycin Sulfate 3.5 mg /

Polymyxin B Sulfate 5000 units

• First Aid Antibiotic

25 Units / Net Wt 0.5 g (1/57 oz)

Item #93473

Made in China